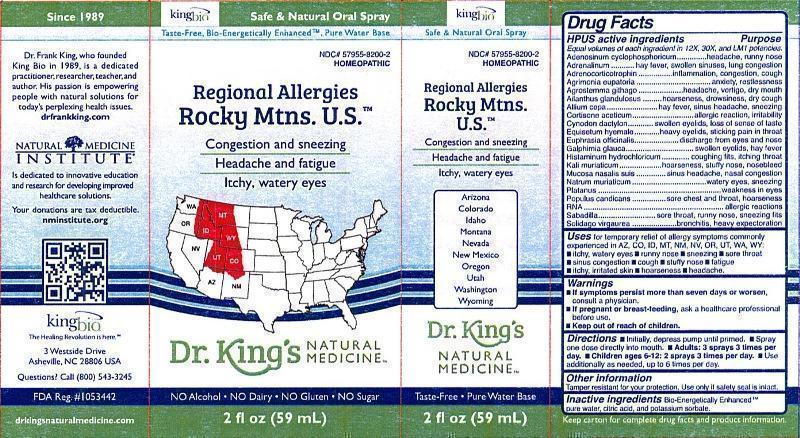 DRUG LABEL: Regional Allergies Rocky Mtns. U.S.
NDC: 57955-8200 | Form: LIQUID
Manufacturer: King Bio Inc.
Category: homeopathic | Type: HUMAN OTC DRUG LABEL
Date: 20131011

ACTIVE INGREDIENTS: ADENOSINE CYCLIC PHOSPHATE 12 [hp_X]/59 mL; EPINEPHRINE 12 [hp_X]/59 mL; CORTICOTROPIN 12 [hp_X]/59 mL; AGRIMONIA EUPATORIA 12 [hp_X]/59 mL; AGROSTEMMA GITHAGO SEED 12 [hp_X]/59 mL; AILANTHUS ALTISSIMA FLOWERING TWIG 12 [hp_X]/59 mL; ONION 12 [hp_X]/59 mL; CORTISONE ACETATE 12 [hp_X]/59 mL; CYNODON DACTYLON 12 [hp_X]/59 mL; EQUISETUM HYEMALE 12 [hp_X]/59 mL; EUPHRASIA STRICTA 12 [hp_X]/59 mL; GALPHIMIA GLAUCA FLOWERING TOP 12 [hp_X]/59 mL; HISTAMINE DIHYDROCHLORIDE 12 [hp_X]/59 mL; POTASSIUM CHLORIDE 12 [hp_X]/59 mL; SUS SCROFA NASAL MUCOSA 12 [hp_X]/59 mL; SODIUM CHLORIDE 12 [hp_X]/59 mL; PLATANUS OCCIDENTALIS WHOLE 12 [hp_X]/59 mL; POPULUS BALSAMIFERA LEAF BUD 12 [hp_X]/59 mL; SACCHAROMYCES CEREVISIAE RNA 12 [hp_X]/59 mL; SCHOENOCAULON OFFICINALE SEED 12 [hp_X]/59 mL; SOLIDAGO VIRGAUREA FLOWERING TOP 12 [hp_X]/59 mL
INACTIVE INGREDIENTS: WATER; CITRIC ACID MONOHYDRATE; POTASSIUM SORBATE

Regional Allergies Rocky Mtns. U.S.™

Drug Facts

____________________________________________________________________________________________________________

HPUS active ingredients: Adenosinum cyclophosphoricum, Adrenalinum, Adrenocorticotrophin, Agrimonia eupatoria, Agrostemma githago, Ailanthus glandulosus, Allium cepa, Cortisone aceticum, Cynodon dactylon, Equisetum hyemale, Euphrasia officinalis, Galphimia glauca, Histaminum hydrochloricum, Kali muriaticum, Mucosa nasalis suis, Natrum muriaticum, Platanus, Populus candicans, RNA, Sabadilla, Solidago virgaurea.

INDICATIONS AND USAGE

Uses for temporary relief of allergy symptoms commonly experienced in AZ, CO, ID, MT, NM, NV, OR, UT, WA, WY:

- itchy, watery eyes
- runny nose
- sneezing
- sore throat
- sinus congestion
- cough
- stuffy nose
- fatigue
- itchy, irritated skin
- hoarseness
- headache

Warnings

- If symptoms persist more than seven days or worsen, consult a physician.
- If pregnant or breast-feeding, ask a healthcare professional before use.

- Keep out of reach of children.

Directions:

- Initially, depress pump until primed.
- Spray one dose directly into mouth.
- Adults: 3 sprays 3 times per day.
- Children ages 6-12: 2 sprays 3 times per day.
- Use additionally as needed, up to 6 times per day.

OTHER SAFETY INFORMATION

Tamper resistant for your protection. Use only if safety seal is intact.

INACTIVE INGREDIENT

Inactive Ingredients: Bio-Energetically Enhanced™ pure water, citric acid and potassium sorbate.

Drug Facts

__________________________________________________________________________________________________________________

HPUS active ingredients Purpose

Equal volumes of each ingredient in 12X, 30X, and LM1 potencies.

Adenosinum cyclophosphoricum........................................................headache, runny nose

Adrenalinum...................................................................................hay fever, swollen sinuses, lung congestion

Adrenocorticotrophin........................................................................inflammation, congestion, cough

Agrimonia eupatoria.........................................................................anxiety, restlessness

Agrostemma githago........................................................................headache, vertigo, dry mouth

Ailanthus glandulosus.......................................................................hoarseness, drowsiness, dry cough

Allium cepa.....................................................................................hay fever, sinus headache, sneezing

Cortisone aceticum...........................................................................allergic reaction, irritability

Cynodon dactylon.............................................................................swollen eyelids, loss of sense of taste

Equisetum hyemale..........................................................................heavy eyelids, sticking pain in throat

Euphrasia officinalis..........................................................................discharge from eyes and nose

Galphimia glauca..............................................................................swollen eyelids, hay fever

Histaminum hydrochloricum...............................................................coughing fits, itching throat

Kali muriaticum................................................................................hoarseness, stuffy nose, nosebleed

Mucosa nasalis suis...........................................................................sinus headache, nasal congestion

Natrum muriaticum...........................................................................watery eyes, sneezing

Platanus...........................................................................................weakness in eyes

Populus candicans..............................................................................sore chest and throat, hoarseness

RNA.................................................................................................allergic reactions

Sabadilla...........................................................................................sore throat, runny nose, sneezing fits

Solidago virgaurea..............................................................................bronchitis, heavy expectoration